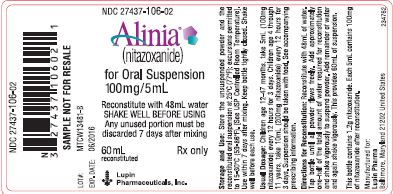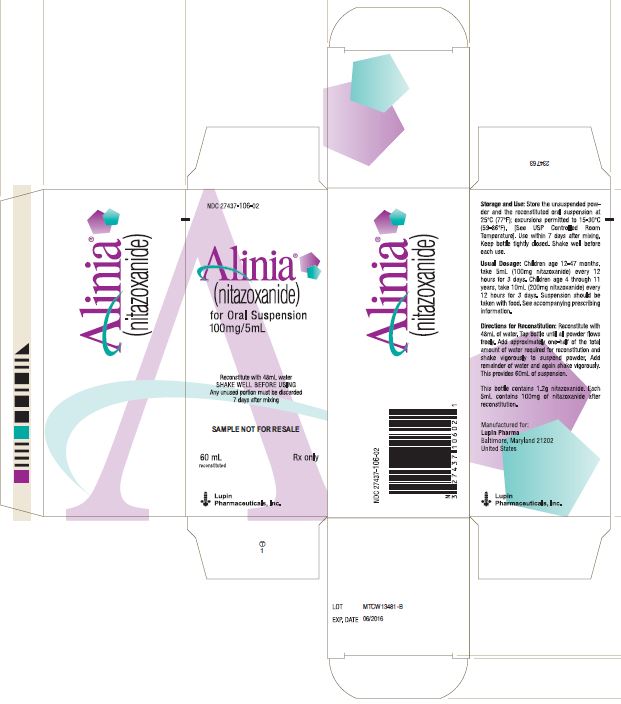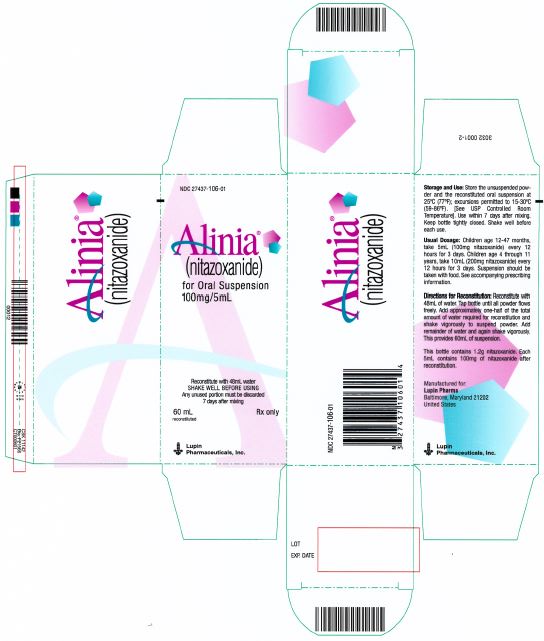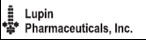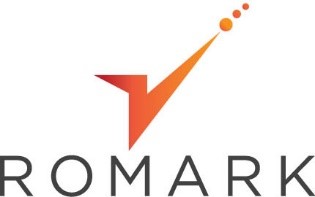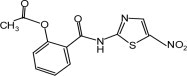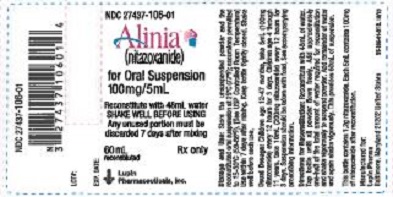 DRUG LABEL: Alinia
NDC: 27437-106 | Form: POWDER, FOR SUSPENSION
Manufacturer: LUPIN PHARMACEUTICALS, INC.
Category: prescription | Type: HUMAN PRESCRIPTION DRUG LABEL
Date: 20240320

ACTIVE INGREDIENTS: NITAZOXANIDE 100 mg/5 mL
INACTIVE INGREDIENTS: MALTODEXTRIN; TRIACETIN; FD&C RED NO. 40; ANHYDROUS CITRIC ACID; TRISODIUM CITRATE DIHYDRATE; SUCROSE; XANTHAN GUM; CELLULOSE, MICROCRYSTALLINE; CARBOXYMETHYLCELLULOSE SODIUM, UNSPECIFIED FORM; SODIUM BENZOATE; MODIFIED CORN STARCH (1-OCTENYL SUCCINIC ANHYDRIDE)

HIGHLIGHTS OF PRESCRIBING INFORMATION

These highlights do not include all the information needed to use ALINIA safely and effectively. See full prescribing information for ALINIA.
ALINIA® (nitazoxanide) tablets, for oral use
ALINIA® (nitazoxanide) for oral suspension
Initial U.S. Approval: 2002

1 INDICATIONS AND USAGE

ALINIA is an antiprotozoal indicated for the treatment of diarrhea caused by Giardia lamblia or Cryptosporidium parvum (1).

Limitations of Use:

ALINIA has not been shown to be effective for the treatment of diarrhea caused by C. parvum in HIV-infected or immunodeficient patients (1).

2 DOSAGE & ADMINISTRATION

- ALINIA Tablets should not be administered to pediatric patient 11 years of age or younger (2.1)
- Dosage for treatment of diarrhea caused by G. lambliaor C. parvum(2.1):

Age | Dosage | Duration
1-3 years | 5 mL of ALINIA for Oral Suspension (100 mg nitazoxanide) every 12 hours with food
4-11 years | 10 mL of ALINIA for Oral Suspension (200 mg nitazoxanide) every 12 hours with food | 3 days
12 years and older | One ALINIA Tablet (500 mg nitazoxanide) every 12 hours with food or25 mL of ALINIA for Oral Suspension (500 mg nitazoxanide) every 12 hours with food

3 DOSAGE FORMS AND STRENGTHS

- ALINIA Tablets: 500 mg (3.1)
- ALINIA for Oral Suspension: 100 mg/5 mL (3.2)

4 CONTRAINDICATIONS

Hypersensitivity (4.1)

6 ADVERSE REACTIONS

The most common adverse reactions in ≥2% of patients were abdominal pain, headache, chromaturia, and nausea (6.1).

To report SUSPECTED ADVERSE REACTIONS, contact Romark at 813-282-8544 or FDA at 1-800-FDA-1088 or www.fda.gov/medwatch.

7 DRUG INTERACTIONS

Competition for binding sites may occur when administered concurrently with other highly plasma protein-bound drugs with narrow therapeutic indices. Monitor for adverse reactions (7).

8 USE IN SPECIFIC POPULATIONS

Pediatric Patients: Safety and efficacy of ALINIA for Oral Suspension in pediatric patients less than one year of age has not been studied (8.4).

FULL PRESCRIBING INFORMATION

1 INDICATIONS AND USAGE

Diarrhea caused by Giardia lambliaor Cryptosporidium parvum:

ALINIA for Oral Suspension (patients 1 year of age and older) and ALINIA Tablets (patients 12 years and older) are indicated for the treatment of diarrhea caused by Giardia lambliaor Cryptosporidium parvum.

Limitations of Use

ALINIA for Oral Suspension and ALINIA Tablets have not been shown to be effective for the treatment of diarrhea caused by Cryptosporidium parvumin HIV-infected or immunodeficient patients [ see Clinical Studies (14.2)]

2 DOSAGE & ADMINISTRATION

2.1 Recommended Dosage and Important Administration Instructions

Important Administration Instructions for Pediatric Patients 11 years of Age or Younger:

ALINIA tablets should not be administered to pediatric patients 11 years of age or younger because a single tablet contains a greater amount of nitazoxanide than the recommended dosing in this pediatric age group.

Table 1. Recommended Dosage

Age | Dosage | Duration
1-3 years | 5 mL of ALINIA for Oral suspension; (100 mg nitazoxanide) taken orally every 12 hours with food
4-11 years | 10 mL of ALINIA for Oral Suspension; (200 mg nitazoxanide) taken orally every 12 hours with food | 3 Days
12 years and older | One ALINIA Tablet (500 mg nitazoxanide) taken orally every 12 hours with food or25 mL of ALINIA for Oral Suspension (500 mg nitazoxanide) taken orally every 12 hours with food

2.2 Directions for Mixing ALINIA for Oral Suspension

Reconstitute ALINIA for Oral Suspension as follows:

- Measure 48 mL of water for preparation of the 100 mg/5 mL suspension
- Tap bottle until all powder flows freely.
- Add approximately one-half of the 48 mL of water required for reconstitution and shake vigorously to suspend powder.
- Add remainder of water and again shake vigorously

Keep container tightly closed, and shake the suspension well before each administration. The reconstituted suspension may be stored for 7 days at room temperature, after which any unused portion must be discarded.

3 DOSAGE FORMS AND STRENGTHS

3.1 ALINIA Tablets (500 mg)

Round, yellow, film-coated tablets debossed with ALINIA on one side and 500 on the other side. Each tablet contains 500 mg of nitazoxanide.

3.2 ALINIA for Oral Suspension (100 mg/5 mL)

Pink-colored powder formulation that, when reconstituted as directed, contains 100 mg nitazoxanide/5 mL. The reconstituted suspension has a pink color and strawberry flavor.

4 CONTRAINDICATIONS

4.1 Hypersensitivity

ALINIA Tablets and ALINIA for Oral Suspension are contraindicated in patients with a prior hypersensitivity to nitazoxanide or any other ingredient in the formulations.

6 ADVERSE REACTIONS

6.1 Clinical Trials Experience

Because clinical trials are conducted under widely varying conditions, adverse reactions rates observed in the clinical trials of a drug cannot be directly compared to rates in the clinical trials of another drug and may not reflect the rates observed in practice.

The safety of ALINIA was evaluated in 2177 HIV-uninfected subjects 12 months of age and older who received ALINIA Tablets or ALINIA for Oral Suspension at the recommended dose for at least three days. In pooled controlled clinical trials involving 536 HIV-uninfected subjects treated with ALINIA Tablets or ALINIA for Oral Suspension, the most common adverse reactions were abdominal pain, headache, chromaturia and nausea (≥2%).

Safety data were analyzed separately for 280 HIV-uninfected subjects ≥12 years of age receiving ALINIA at the recommended dose for at least three days in 5 placebo-controlled clinical trials and for 256 HIV-uninfected subjects 1 through 11 years of age in 7 controlled clinical trials. There were no differences between the adverse reactions reported for ALINIA-treated subjects based upon age.

6.2 Postmarketing Experience

The following adverse reactions have been identified during post approval use of ALINIA. Because these reactions are reported voluntarily from a population of uncertain size, it is not always possible to reliably estimate their frequency or establish a causal relationship to drug exposure. The following is a list of adverse reactions spontaneously reported with ALINIA Tablets which were not included in clinical trial listings:

Gastrointestinal disorders:diarrhea, gastroesophageal reflux disease

Nervous System disorders:dizziness

Respiratory, thoracic and mediastinal disorders:dyspnea

Skin and subcutaneous tissue disorders:rash, urticaria

7 DRUG INTERACTIONS

7.1 Highly Protein Bound Drugs with Narrow Therapeutic Indices

Tizoxanide (the active metabolite of nitazoxanide) is highly bound to plasma protein (>99.9%). Therefore, monitor for adverse reactions when administering nitazoxanide concurrently with other highly plasma protein-bound drugs with narrow therapeutic indices, as competition for binding sites may occur (e.g., warfarin).

8 USE IN SPECIFIC POPULATIONS

8.1 Pregnancy

Risk Summary

There are no data with ALINIA in pregnant women to inform a drug-associated risk. No teratogenicity or fetotoxicity was observed in animal reproduction studies with administration of nitazoxanide to pregnant rats and rabbits during organogenesis at exposure 30 and 2 times, respectively, the exposure at the maximum recommended human dose of 500 mg twice daily based on body surface area (BSA).

In the U.S. general population, the estimated background risk of major birth defects and miscarriage in clinically recognized pregnancies is 2% to 4% and 15% to 20%, respectively.

Data

Animal Data

Nitazoxanide was administered orally to pregnant rats at doses of 0, 200, 800 or 3200 mg/kg/day on gestation days 6 to 15. Nitazoxanide produced no evidence of systemic maternal toxicity when administer once daily via oral gavage to pregnant female rats at levels up to 3200 mg/kg/day during the period of organogenesis .

In rabbits, nitazoxanide was administered at doses of 0, 25, 50, or 100 mg/kg/day on gestation days 7 to 20. Oral treatment of pregnant rabbits with nitazoxanide during organogenesis resulted in minimal maternal toxicity and no external fetal anomalies.

8.2 Lactation

Risk Summary

No information regarding the presence of nitazoxanide in human milk, the effects on the breastfed infant, or the effects on milk production is available. The development and health benefits of breastfeeding should be considered along with the mother’s clinical need for ALINIA and any potential adverse effects on the breastfed infant from ALINIA or from the underlying maternal condition.

8.4 Pediatric Use

The safety and efficacy of ALINIA for Oral Suspension for the treatment of diarrhea caused by G. lambliaor C. parvumin pediatric patients 1 to 11 years of age has been established based on three (3) randomized, controlled studies with 104 pediatric subjects treated with ALINIA for Oral Suspension 100 mg/5 mL. Furthermore, the safety and efficacy of ALINIA for Oral Suspension for the treatment of diarrhea caused by G. lambliaor C. parvumin pediatric patients 12 to 17 years of age has been established based on two (2) randomized controlled studies with 44 pediatric subjects treated with ALINIA for Oral Suspension 100 mg/5 mL. [ see Clinical Studies (14.1)]

The safety and efficacy of ALINIA Tablets for the treatment of diarrhea caused by G. lambliaor C. parvumin pediatric patients 12 to 17 years of age has been established based on three (3) randomized controlled studies with 47 pediatric subjects treated with ALINIA Tablets 500 mg.

A single ALINIA Tablet contains a greater amount of nitazoxanide than is recommended for use in pediatric patients 11 years or younger. [ see Dosage and Administration (2.1)].

Safety and efficacy of ALINIA for Oral Suspension in pediatric patients less than one year of age has not been studied.

8.5 Geriatric Use

Clinical studies of ALINIA Tablets and ALINIA for Oral Suspension did not include sufficient numbers of subjects aged 65 and over to determine whether they respond differently from younger subjects. In general, the greater frequency of decreased hepatic, renal, or cardiac function, and of concomitant disease or other drug therapy in elderly patients should be considered when prescribing ALINIA Tablets and ALINIA for Oral Suspension.

8.6 Renal and Hepatic Impairment

The pharmacokinetics of nitzoxanide in patients with compromised renal or hepatic function has not been studied.

8.7 HIV-Infected or Immunodeficient Patients

ALINIA Tablets and ALINIA for Oral Suspension have not been studied for the treatment of diarrhea caused by G. lamblia in HIV-infected or immunodeficient patients. ALINIA Tablets and ALINIA for Oral Suspension have not been shown to be superior to placebo for the treatment of diarrhea caused by C. parvum in HIV-infected or immunodeficient patients [ see Clinical Studies (14)]

10 OVERDOSAGE

Limited information on nitazoxanide overdosage is available. Single oral doses of up to 4000 mg nitazoxanide have been administered to healthy adult volunteers without significant adverse effects. In the event of overdose, gastric lavage may be appropriate soon after oral administration. Patients should be observed and given symptomatic and supportive treatment. There is no specific antidote for overdose with ALINIA. Because tizoxanide is highly protein bound (>99.9%), dialysis is unlikely to significantly reduce plasma concentrations of the drug.

11 DESCRIPTION

ALINIA Tablets and ALINIA for Oral Suspension contain the active ingredient, nitazoxanide, a synthetic antiprotozoal for oral administration. Nitazoxanide is a light yellow crystalline powder. It is poorly soluble in ethanol and practically insoluble in water. Chemically, nitazoxanide is 2-acetyloxy- N-(5-nitro-2-thiazolyl)benzamide. The molecular formula is C12H9N3O5S and the molecular weight is 307.3. The structural formula is:

ALINIA Tablets contain 500 mg of nitazoxanide and the following inactive ingredients: maize starch, pregelatinized corn starch, hydroxypropyl methylcellulose, sucrose, sodium starch glycollate, talc, magnesium stearate, soy lecithin, polyvinyl alcohol, xanthan gum, titanium dioxide, FD&C Yellow No. 10 Aluminum Lake, FD&C Yellow No. 6 Aluminum Lake, and FD&C Blue No. 2 Aluminum Lake.

ALINIA for Oral Suspension, when reconstituted with 48 mL of water, produces 60 mL of a homogeneous suspension with a pink color that contains 100 mg nitazoxanide per 5 mL and the following inactive ingredients: sodium benzoate, sucrose, xanthan gum, microcrystalline cellulose and carboxymethylcellulose sodium, anhydrous citric acid, sodium citrate dihydrate, maltodextrin, modified food starch, triacetin, FD&C Red No. 40 and artificial strawberry flavoring.

12 CLINICAL PHARMACOLOGY

12.1 Mechanism of Action

Nitazoxanide is an antiprotozoal [ see Microbiology (12.4))].

12.3 Pharmacokinetics

Absorption

Single Dosing:

Following oral administration of ALINIA Tablets or Oral Suspension, the parent drug, nitazoxanide, is not detected in plasma. The pharmacokinetic parameners of the metabolites, tizoxanide and tizoxanide glucuronide are shown in Tables 2 and 3 below.

Table 2. Mean (+/- SD) plasma pharmacokinetic parameters of tizoxanide and tizoxanide glucuronide following administration of a single dose of one 500 mg ALINIA Tablet with food to subjects ≥12 years of age

 | Tizoxanide |  |  | Tizoxanide Glucuronide
Age | Cmax(µg/mL) | *Tmax(hr) | AUCt(µg•hr/mL) | Cmax(µg/mL) | *Tmax(hr) | AUCt(µg•hr/mL)
12 - 17 years | 9.1 (6.1) | 4.0 (1-4) | 39.5 (24.2) | 7.3 (1.9) | 4.0 (2-8) | 46.5 (18.2)
>18 years | 10.6 (2.0) | 3.0 (2-4) | 41.9 (6.0) | 10.5 (1.4) | 4.5 (4-6) | 63.0 (12.3)

*Tmaxis given as a Mean (Range)

Table 3. Mean (+/-SD) plasma pharmacokinetic of tizoxanide and tizoxanide glucuronide parameter values following administration of single dose of ALINIA for Oral Suspension with food to subjects ≥1year of age

 |  | Tizoxanide |  |  | Tizoxanide Glucuronide
Age | Dose | Cmax(µg/mL) | *Tmax(hr) | AUCt(µg•hr/mL) | Cmax(µg/mL) | *Tmax(hr) | AUCinf(µg•hr/mL)
1-3 years | 100 mg | 3.11 (2.0) | 3.5 (2-4) | 11.7 (4.46) | 3.64 (1.16) | 4.0 (3-4) | 19.0 (5.03)
4-11 years | 200 mg | 3.00 (0.99) | 2.0 (1-4) | 13.5 (3.3) | 2.84 (0.97) | 4.0 (2-4) | 16.9 (5.00)
>18 years | 500 mg | 5.49 (2.06) | 2.5 (1-5) | 30.2 (12.3) | 3.21 (1.05) | 4.0 (2.5-6) | 22.8 (6.49)

*Tmaxis given as a Mean (Range)

Multiple dosing:

Following oral administration of a single ALINIA Tablet every 12 hours for 7 consecutive days, there was no significant accumulation of nitazoxanide metabolites tizoxanide or tizoxanide glucuronide detected in plasma.

Bioavailability:

ALINIA for Oral Suspension is not bioequivalent to ALINIA Tablets. The relative bioavailability of the suspension compared to the tablet was 70%.

When ALINIA Tablets are administered with food, the AUCtof tizoxanide and tizoxanide glucuronide in plasma is increased almost two-fold and the Cmaxis increased by almost 50%.

When ALINIA for Oral Suspension was administered with food, the AUCtof tizoxanide and tizoxanide glucuronide increased by about 45-50% and the Cmaxincreased by ≤10%.

ALINIA Tablets and ALINIA for Oral Suspension were administered with food in clinical trials and hence they are recomended to be administered with food [see Dosage and Administration (2.1)]

Distribution

In plasma, more than 99% of tizoxanide is bound to proteins.

Elimination

Metabolism

Following oral administration in humans, nitazoxanide is rapidly hydrolyzed to an active metabolite, tizoxanide (desacetyl-nitazoxanide). Tizoxanide then undergoes conjugation, primarily by glucuronidation.

Excretion

Tizoxanide is excreted in the urine, bile and feces, and tizoxanide glucuronide is excreted in urine and bile. Approximately two-thirds of the oral dose of nitazoxanide is excreted in the feces and one-third in the urine.

Specific Populations

Pediatric Patients

The pharmacokinetics of tizoxanide and tizoxanide glucuronide following administration of ALINIA Tablets in pediatric patients 12-17 years of age are provided above in Table 2. The pharmacokinetics of tizoxanide and tizoxanide glucuronide following administration of ALINIA for Oral Suspension in pediatric patients 1-11 years of age are provided above in Table 3.

Drug Interaction Studies

In vitrostudies have demonstrated that tizoxanide has no significant inhibitory effect on cytochrome P450 enzymes.

12.4 MICROBIOLOGY

Mechanism of Action

The antiprotozoal activity of nitazoxanide is believed to be due to interference with the pyruvate:ferredoxin oxidoreductase (PFOR) enzyme-dependent electron transfer reaction which is essential to anaerobic energy metabolism. Studies have shown that the PFOR enzyme from G. lambliadirectly reduces nitazoxanide by transfer of electrons in the absence of ferredoxin. The DNA-derived PFOR protein sequence of C. parvumappears to be similar to that of G. lamblia. Interference with the PFOR enzyme-dependent electron transfer reaction may not be the only pathway by which nitazoxanide exhibits antiprotozoal activity.

Resistance

A potential for development of resistance by C. parvumor G. lambliato nitazoxanide has not been examined.

Antimicrobial Activity

Nitazoxanide and its metabolite, tizoxanide, are active in vitroin inhibiting the growth of (i) sporozoites and oocysts of C. parvumand (ii) trophozoites of G. lamblia.

Susceptibility Test Methods

For protozoa such as C. parvumand G. lamblia, standardized tests for use in clinical microbiology laboratories are not available.

13 NONCLINICAL TOXICOLOGY

13.1 Carcinogenesis, Mutagenesis, Impairment of Fertility

Carcinogenesis

Long-term carcinogenicity studies have not been conducted.

Mutagenesis

Nitazoxanide was not genotoxic in the Chinese hamster ovary (CHO) cell chromosomal aberration assay or the mouse micronucleus assay. Nitazoxanide was genotoxic in one tester strain (TA100) in the Ames bacterial mutation assay.

Impairment of Fertility

Nitazoxanide did not adversely affect male or female fertility in the rat at 2400 mg/kg/day (approximately 20 times the clinical adult dose adjusted for body surface area).

14 CLINICAL STUDIES

14.1 Diarrhea Caused by G. lamblia

Diarrhea caused by G. lambliain adults and adolescents 12 years of age or older:

In a double-blind, controlled trial (Study 1) conducted in Peru and Egypt in adults and adolescents with diarrhea and with one or more enteric symptoms (e.g., abdominal pain, nausea, vomiting, fever, abdominal distention, loss of appetite, flatulence) caused by G. lamblia, a three-day course of treatment with ALINIA Tablets administered 500 mg BID was compared with a placebo tablet for 3 days. A third group of patients received open-label ALINIA for Oral Suspension administered 500 mg/25 mL of suspension BID for 3 days. A second double-blind, controlled trial (Study 2) conducted in Egypt in adults and adolescents with diarrhea and with or without enteric symptoms (e.g., abdominal colic, abdominal tenderness, abdominal cramps, abdominal distention, fever, bloody stool) caused by G. lambliacompared ALINIA Tablets administered 500 mg BID for 3 days to a placebo tablet. For both of these studies, clinical response was evaluated 4 to 7 days following the end of treatment. A clinical response of ‘well’ was defined as ‘no symptoms, no watery stools and no more than 2 soft stools with no hematochezia within the past 24 hours’ or ‘no symptoms and no unformed stools within the past 48 hours.’ The following clinical response rates were obtained:

Table 4. Adult and Adolescent Patients with Diarrhea Caused by G. lamblia

Clinical Response Rates* 4 to 7 Days Post-therapy

% (Number of Successes/Total)

 | ALINIA Tablets | ALINIA for Oral Suspension | Placebo Tablets
Study 1 | 85% (46/54)¶ § | 83% (45/54)¶ § | 44% (12/27)
Study 2 | 100% (8/8) | - | 30% (3/10)

* Includes all patients randomized with G. lambliaas the sole pathogen. Patients failing to complete the studies were treated as failures.

¶Clinical response rates statistically significantly higher when compared to placebo.

§The 95% confidence interval of the difference in response rates for the tablet and suspension is (-14%, 17%).

Some patients with ‘well’ clinical responses had G. lambliacysts in their stool samples 4 to 7 days following the end of treatment. The relevance of stool examination results in these patients is unknown. Patients should be managed based upon clinical response to treatment.

Diarrhea caused by G. lambliain pediatric patients 1 through 11 years of age:

In a randomized, controlled trial conducted in Peru in 110 pediatric patients with diarrhea and with or without enteric symptoms (e.g., abdominal distention, right iliac fossa tenderness) caused by G. lamblia, a three-day course of treatment with nitazoxanide (100 mg BID in pediatric patients ages 24-47 months, 200 mg BID in pediatric patients ages 4 through 11 years) was compared to a five-day course of treatment with metronidazole (125 mg BID in pediatric patients ages 2 through 5 years, 250 mg BID in pediatric patients ages 6 through 11 years). Clinical response was evaluated 7 to 10 days following initiation of treatment with a ‘well’ response defined as ‘no symptoms, no watery stools and no more than 2 soft stools with no hematochezia within the past 24 hours’ or ‘no symptoms and no unformed stools within the past 48 hours.’ The following clinical cure rates were obtained:

Table 5. Clinical Response Rates in Pediatric Patients 7 to 10 Days Following Initiation of Therapy

Intent-to-Treat and Per Protocol Analyses

% (Number of Successes/Total), [95% Confidence Interval]

Population | Nitazoxanide (3 days) | Metronidazole (5 days) | 95% CIDiff§
Intent-to-treat analysis† | 85% (47/55) | 80% (44/55) | [-9%, 20%]
Per protocol analysis ¶ | 90% (43/48) | 83% (39/47) | [-8%, 21%]

†Intent-to-treat analysis includes all patients randomized with patients not completing the study treated as failures.

¶Per protocol analysis includes only patients who took all of their medication and completed the study. Seven patients in each treatment group missed at least one dose of medication and one in the metronidazole treatment group was lost to follow-up.

§95% Confidence Interval on the difference in response rates (nitazoxanide-metronidazole).

Some patients with ‘well’ clinical responses had G. lambliacysts in their stool samples 4 to 7 days following the end of treatment. The relevance of stool examination results in these patients is unknown. Patients should be managed based upon clinical response to treatment.

14.2 Diarrhea Caused by C. parvum

Diarrhea caused by C. parvumin adults and adolescents 12 years of age or older:

In a double-blind, controlled trial conducted in Egypt in adults and adolescents with diarrhea and with or without enteric symptoms (e.g., abdominal pain/cramps, nausea, vomiting) caused by C. parvum, a three-day course of treatment with ALINIA Tablets administered 500 mg BID was compared with a placebo tablet for 3 days. A third group of patients received open-label ALINIA for Oral Suspension administered 500 mg/25 mL of suspension BID for 3 days. Clinical response was evaluated 4 to 7 days following the end of treatment. A clinical response of ‘well’ was defined as ‘no symptoms, no watery stools and no more than 2 soft stools within the past 24 hours’ or ‘no symptoms and no unformed stools within the past 48 hours.’ The following clinical response rates were obtained:

Table 6. Clinical Response Rates in Adult and Adolescent Patients 4 to 7 Days Post-therapy

% (Number of Successes/Total)

 | ALINIA Tablets | ALINIA Suspension | Placebo Tablets
Intent-to-treat analysis* | 96% (27/28)¶ § | 87% (27/31)¶ § | 41% (11/27)

* Includes all patients randomized with C. parvumas the sole pathogen. Patients failing to complete the study were treated as failures.

¶Clinical response rates statistically significantly higher when compared to placebo.

§The 95% confidence interval of the difference in response rates for the tablet and suspension is (-10%, 28%).

In a second double-blind, placebo-controlled study of nitazoxanide tablets conducted in Egypt in adults and adolescents with diarrhea and with or without enteric symptoms (e.g., abdominal colic, abdominal cramps, epigastric pain) caused by C. parvumas the sole pathogen, clinical and parasitological response rates showed a similar trend to the first study. Clinical response rates, evaluated 2 to 6 days following the end of treatment, were 71% (15/21) in the nitazoxanide group and 42.9% (9/21) in the placebo group.

Some patients with ‘well’ clinical responses had C. parvumoocysts in their stool samples 4 to 7 days following the end of treatment. The relevance of stool examination results in these patients is unknown. Patients should be managed based upon clinical response to treatment.

Diarrhea caused by C. parvumin pediatric patients 1 through 11 years of age :

In two double-blind, controlled trials in pediatric patients with diarrhea and with or without enteric symptoms (e.g., abdominal distention, colic, left iliac fossa tenderness) caused by C. parvum, a three-day course of treatment with nitazoxanide (100 mg BID in pediatric patients ages 12-47 months, 200 mg BID in pediatric patients ages 4 through 11 years) was compared with a placebo. One study was conducted in Egypt in outpatients ages 1 through 11 years with diarrhea caused by C. parvum. Another study was conducted in Zambia in malnourished pediatric patients admitted to the hospital with diarrhea caused by C. parvum. Clinical response was evaluated 3 to 7 days post-therapy with a ‘well’ response defined as ‘no symptoms, no watery stools and no more than 2 soft stools within the past 24 hours’ or ‘no symptoms and no unformed stools within the past 48 hours.’ The following clinical response rates were obtained:

Table 7. Clinical Response Rates in Pediatric Patients 3 to 7 Days Post-therapy Intent-to-Treat Analyses

% (Number of Successes/Total)

Population | Nitazoxanide* | Placebo
Outpatient Study, age 1 - 11 years | 88% (21/24) | 38% (9/24)
Inpatient Study, Malnourished ¶, age 12-35 months | 56% (14/25) | 23% (5/22)

*Clinical response rates statistically significantly higher compared to placebo.

¶60% considered severely underweight, 19% moderately underweight, 17% mild underweight.

Some patients with ‘well’ clinical responses had C. parvumoocysts in their stool samples 3 to 7 days following the end of treatment. The relevance of stool examination results in these patients is unknown. Patients should be managed based upon clinical response to treatment.

Diarrhea caused by C. parvumin Acquired Immune Deficiency Syndrome (AIDS) patients :

A double-blind, placebo-controlled trial did not produce clinical cure rates that were significantly different from the placebo control when conducted in hospitalized, severely malnourished pediatric patients with acquired immune deficiency syndrome (AIDS) in Zambia. In this study, the pediatric patients received a three day course of nitazoxanide suspension (100 mg BID in pediatric patients ages 12-47 months, 200 mg BID in pediatric patients ages 4 through 11 years) and were evaluated for response four days after the end of treatment.

16 HOW SUPPLIED

16.1 ALINIA Tablets (500 mg)

ALINIA tablets are round, yellow, film-coated tablets debossed with ALINIA on one side and 500 on the other side. Each tablet contains 500 mg of nitazoxanide. The tablets are packaged in HDPE bottles of 12 and 30 tablets.

Bottles of 12 tablets NDC 67546-111-14

Bottles of 30 tablets NDC 67546-111-12

Store the tablets at 25oC (77oF); excursions permitted to 15oC-30oC (59oF-86oF). [See USP Controlled Room Temperature]

16.2 ALINIA for Oral Suspension (100 mg/5 mL)

ALINIA for oral suspension is a pink-colored powder formulation that, when reconstituted as directed, contains 100 mg nitazoxanide/5 mL. The reconstituted suspension has a pink color and strawberry flavor. Alinia for oral suspension is available as:

Bottles of 60 mL NDC 27437-106-01

Store the unsuspended powder at 25oC (77oF); excursions permitted to 15oC-30oC (59oF-86oF). [See USP Controlled Room Temperature]

The reconstituted suspension may be stored for 7 days at room temperature, after which any unused portion must be discarded [see Dosage and Administration (2.2)]

17 PATIENT COUNSELING INFORMATION

Advise patients and parents/caregivers of pediatric patients taking ALINIA Tablets or ALINIA for Oral Suspension of the following information:

Dosage and Administration:

ALINIA Tablets and ALINIA for Oral Suspension should be taken with food.

ALINIA for Oral Suspension: The container should be kept tightly closed, and the suspension should be shaken well before each administration. The suspension may be stored at room temperature for 7 days, after which any unused portion must be discarded.

Drug-drug Interactions:

Avoid concurrent warfarin use.

MANUFACTURER INFORMATION

Romark, L.C.
3000 Bayport Drive, Suite 200, Tampa, FL 33607
Telephone: 813-282-8544, Fax: 813-282-1162
E-mail: customer.service@romark.com
Web site: www.romark.com

ALINIA for Oral Suspension is distributed by Lupin Pharmaceuticals, Inc. under license from Romark.

Lupin Pharma

Baltimore, Maryland 21202 United States

US Patents No. 5,578,621; 6,020,353; 5,968,961; 5,387,598; 6,117,894; 5,965,590.

ALINIA is a registered trademark of Romark.

PI-111/106-04 R.07/16

Alinia (nitazoxanide) for Oral Suspension- Carton

NDC 27437-106-01

Alinia®

(nitazoxanide) for Oral Suspension 100 mg/5 mL

Reconstitute with 48 mL water

SHAKE WELL BEFORE USING

Any unused portion must be discarded

60 mL reconstituted Rx only

Lupin Pharmaceuticals, Inc.

Alinia (nitazoxanide) for Oral Suspension- Carton - Sample

NDC 27437-106-02

Alinia® (nitazoxanide) for Oral Suspension

100 mg/5 mL

Reconstitute with 48 mL water

SHAKE WELL BEFORE USING

Any unused portion must be discarded 7 days after mixing

SAMPLE NOT FOR RESALE

60 mL reconstituted Rx only

Lupin Pharmaceuticals, Inc.

Alinia (nitazoxanide) for Oral Suspension - Label- Sample

NDC 27437-106-02

Alinia® (nitazoxanide) for Oral Suspension

100 mg/5 mL

Reconstitute with 48 mL water

SHAKE WELL BEFORE USING

Any unused portion must be discarded 7 days after mixing

SAMPLE NOT FOR RESALE

60 mL reconstituted Rx only

Lupin Pharmaceuticals, Inc.

Alinia for Oral Suspension - Label

NDC 27437-106-01

Alinia (nitazoxanide) for Oral Suspension 100 mg/5 mL

Reconstitute with 48 mL water

SHAKE WELL BEFORE USING

Any unused portion must b discarded 7 days after mixing

60 mL reconstituted Rx only

Lupin Pharmaceuticals, Inc.